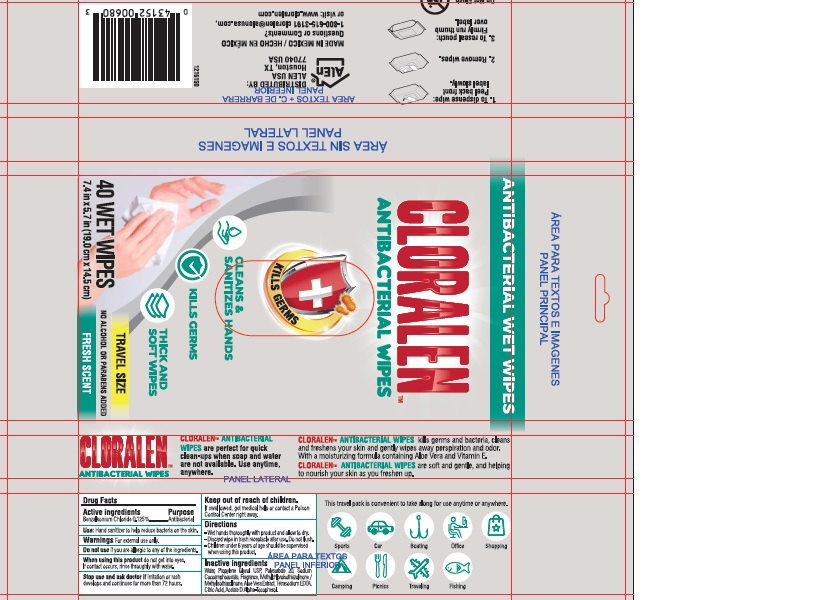 DRUG LABEL: CLORALEN TM ANTIBACTERIAL WIPES
NDC: 70697-802 | Form: LIQUID
Manufacturer: INDELPA, S.A DE C.V
Category: otc | Type: HUMAN OTC DRUG LABEL
Date: 20220113

ACTIVE INGREDIENTS: BENZALKONIUM CHLORIDE 0.125 mg/100 mg
INACTIVE INGREDIENTS: ALPHA-TOCOPHEROL ACETATE 0.01 mg/100 mg; EDETATE SODIUM 0.03 mg/100 mg; WATER 98.567 mg/100 mg; METHYLCHLOROISOTHIAZOLINONE/METHYLISOTHIAZOLINONE MIXTURE 0.1 mg/100 mg; ALOE VERA LEAF 0.05 mg/100 mg; CITRIC ACID MONOHYDRATE 0.018 mg/100 mg; FRAGRANCE CLEAN ORC0600327 0.1 mg/100 mg; POLYSORBATE 20 0.3 mg/100 mg; SODIUM COCOAMPHOACETATE 0.2 mg/100 mg; PROPYLENE GLYCOL 0.05 mg/100 mg

PURPOSE

Antibacterial

ACTIVE INGREDIENT

BENZALKONIUM, CHLORIDE 0.125%

INDICATIONS AND USAGE

Hand sanitizer to help reduce bacteria on the skin

WARNINGS

For external use only.

DO NOT USE

If you are allergic to any of the ingredients

WHEN USING

Do not get into eyes.

If contact occurs, rinse throughly with water

STOP USE

If irritation or rash develops and continues for more than 72 hours

ASK DOCTOR

If irritation or rash develops and continues for more than 72 hours

KEEP OUT OF REACH OF CHILDREN

If swallowed, get medical help or contact a Poison Control Center right away

INSTRUCTIONS FOR USE

- wet hands throughly with product and allow to dry.

-discard wipe in trash receptacle after use. Do not flush

- chuldren under 6 years af age should be supervised whe using this product

INACTIVE INGREDIENT

water, propylene glycol USP, polysorbate 20, sodium cocoamphoacetate, fragrance, methylchloroisothiazolinone / methylisothiazolinone, aloe vera extract, tetrasodium EDTA, citric acid, acetate D alpha- tocopherol

DOSAGE AND ADMINISTRATION

Topical admistration